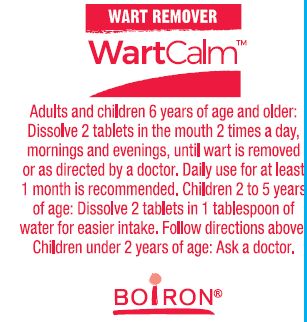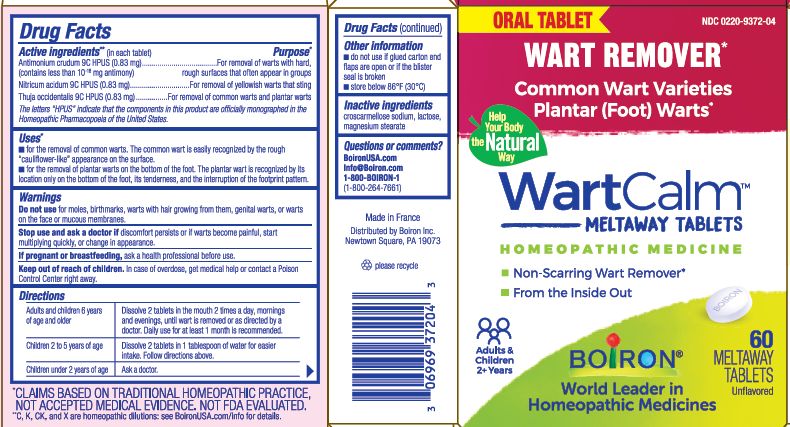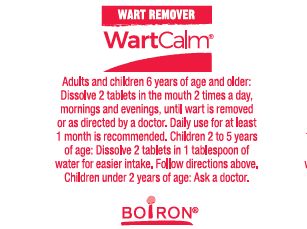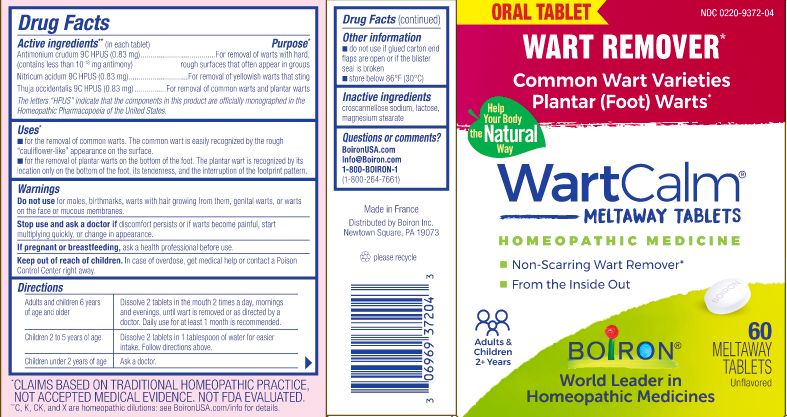 DRUG LABEL: WartCalm
NDC: 0220-9372 | Form: TABLET
Manufacturer: Boiron
Category: homeopathic | Type: HUMAN OTC DRUG LABEL
Date: 20230413

ACTIVE INGREDIENTS: ANTIMONY TRISULFIDE 9 [hp_C]/1 1; THUJA OCCIDENTALIS LEAFY TWIG 9 [hp_C]/1 1; NITRIC ACID 9 [hp_C]/1 1
INACTIVE INGREDIENTS: LACTOSE, UNSPECIFIED FORM; CROSCARMELLOSE SODIUM; MAGNESIUM STEARATE

WartCalm Tablets

Active ingredients ** (in each tablet)

Antimonium crudum 9C HPUS (0.83 mg) (contains less than 10^-18 mg antimony)

Nitricum acidum 9C HPUS (0.83 mg)

Thuja occidentalis 9C HPUS (0.83 mg)

The letters "HPUS" indicate that the components in this product are officially monographed in the Homeopathic Pharmacopoeia of the United States.

Purpose*

Antimonium crudum 9C HPUS (0.83 mg) ... For removal of warts with hard, rough surfaces that often appear in groups

Nitricum acidum 9C HPUS (0.83 mg) ... For removal of yellowish warts that sting

Thuja occidentalis 9C HPUS ... For removal of common warts and plantar warts

Uses*

- for the removal of common warts. The common wart is easily recognized by the rough "cauliflower-like" appearance on the surface.
- for the removal of plantar warts on the bottom of the foot. The plantar wart is recognized by its location only on the bottom of the foot, its tenderness, and the interruption of the footprint pattern.

Warnings

Do not use for moles, birthmarks, warts with hair growing on them, genital warts, or warts on the face or mucous membranes.

Stop use and ask a doctor if discomfort persists or if warts become painful, start multiplying quickly, or change in appearance.

PREGNANCY OR BREAST FEEDING

If pregnant or breastfeeding, ask a health professional before use.

Keep out of reach of children. In case of overdose, get medical help or contact a Poison Control Center right away.

Directions

Adults and children 6 years of age and older - Dissolve 2 tablets in the mouth 2 times a day, mornings and evenings, until wart is removed or as directed by a doctor. Daily use for at least 1 month is recommended.

Children 2 to 5 years of age - Dissolve 2 tablets in 1 tablespoon of water for easier intake. Follow directions above.

Children under 2 years of age - Ask a doctor.

Other information

- do not use if glued carton and flaps are open or if the blister seal is broken
- store below 86° F (30° C)

INACTIVE INGREDIENT

croscarmellose sodium, lactose, magnesium stearate

QUESTIONS

BoironUSA.com

Info@Boiron.com

1-800-BOIRON-1

(1-800-264-7661)

Made in France

Distributed by Boiron Inc.

Newtown Square, PA 19073

Wart Remover*

Common Wart Varieties Planter (Foot) Warts*

Non-scarring Wart Remover*

From the Inside Out

60 meltaway tablets unflavored

Meltaway Tablets Require No Food or Water

No Artificial Colors, Flavors, Sweeteners, or Preservatives

No Known Drug Interactions

*CLAIMS BASED ON TRADITIONAL HOMEOPATHIC PRACTICE, NOT ACCEPTED MEDICAL EVIDENCE. NOT FDA EVALUATED.
*C,K,CK, and X are homeopathic dilutions: see BoironUSA.com/info for details.